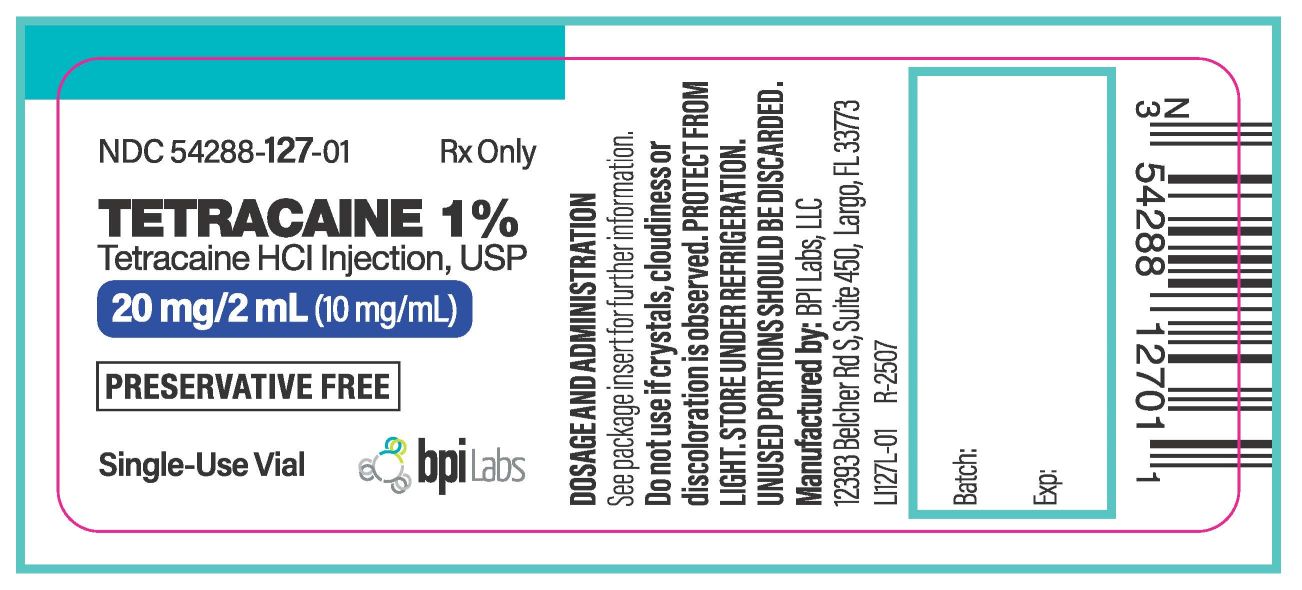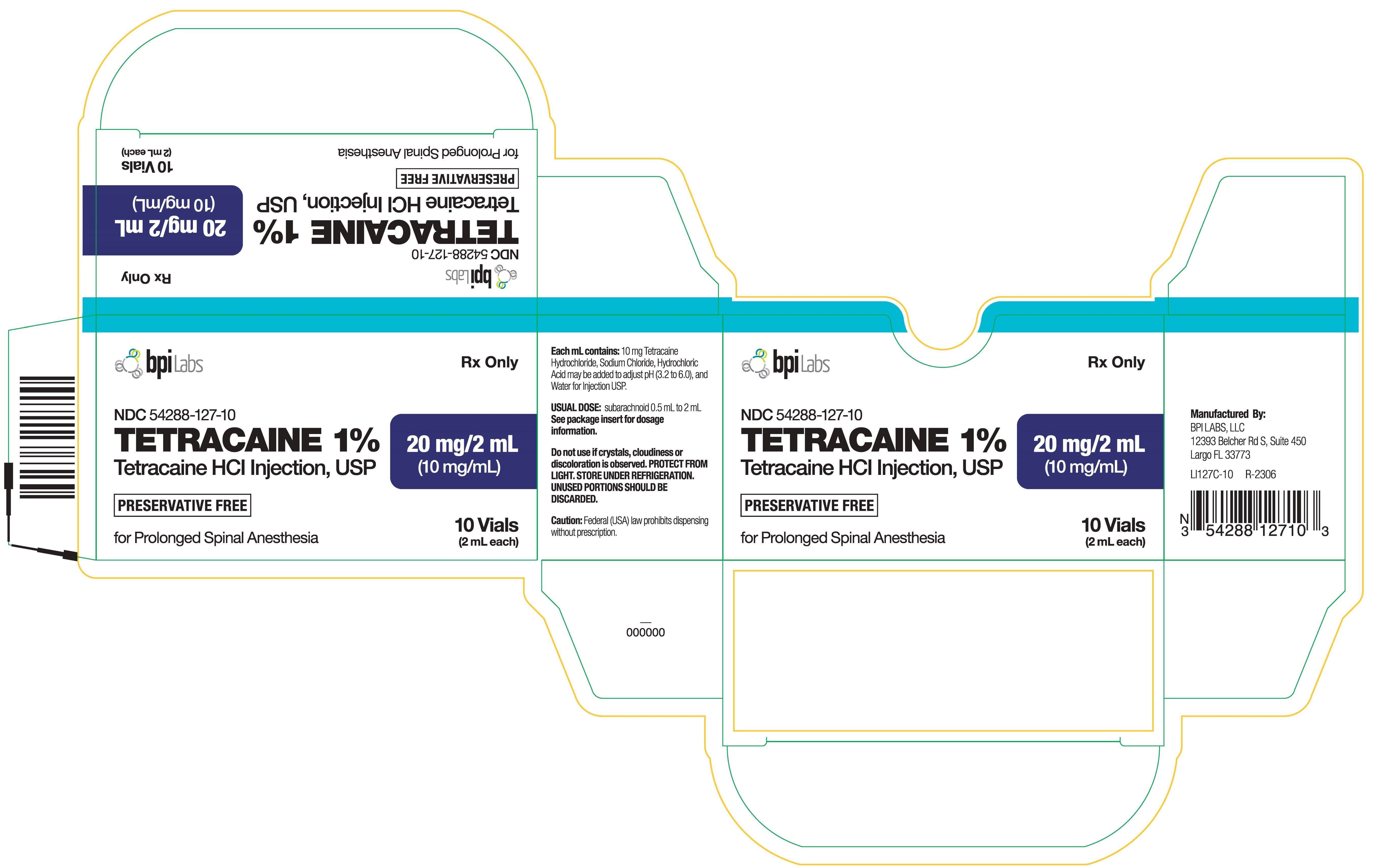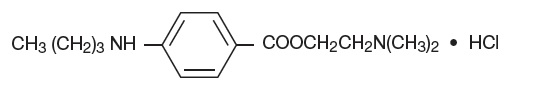 DRUG LABEL: Tetracaine HCL
NDC: 54288-127 | Form: INJECTION
Manufacturer: BPI LABS LLC
Category: prescription | Type: HUMAN PRESCRIPTION DRUG LABEL
Date: 20251217

ACTIVE INGREDIENTS: TETRACAINE HYDROCHLORIDE 10 mg/1 mL
INACTIVE INGREDIENTS: SODIUM CHLORIDE; HYDROCHLORIC ACID; SODIUM HYDROXIDE; WATER

TETRACAINE 1%
Tetracaine HCl Injection, USP
for Prolonged Spinal Anesthesia
BPI Labs, LLC
Rx Only

DESCRIPTION

Tetracaine hydrochloride is 2-(Dimethylamino)ethyl p-(butylamino)benzoate monohydrochloride. It is a white crystalline, odorless powder that is readily soluble in water, physiologic saline solution, and dextrose solution. It has the following structural formula:

Tetracaine hydrochloride is a local anesthetic of the ester-linkage type, related to procaine.

1% Solution: A sterile, isotonic, isobaric solution.

Each mL contains:
Active: 10 mg Tetracaine Hydrochloride
Inactives: 7.5 mg Sodium Chloride, Hydrochloric Acid may be added to adjust pH (3.2 to 6.0) and Water for Injection, USP.

Nitrogen gas has been used to displace the air in the vials.

This formulation does not contain preservatives.

CLINICAL PHARMACOLOGY:

Parenteral administration of tetracaine hydrochloride stabilizes the neuronal membrane and prevents initiation and transmission of nerve impulses thereby effecting local anesthesia.

The onset of action is rapid, and the duration is prolonged (up to two or three hours or longer of surgical anesthesia).

Tetracaine hydrochloride is detoxified by plasma esterases to aminobenzoic acid and diethylaminoethanol.

INDICATIONS AND USAGE:

Tetracaine hydrochloride is indicated for the production of spinal anesthesia for procedures requiring two to three hours.

CONTRAINDICATIONS:

Spinal anesthesia with tetracaine hydrochloride is contraindicated in patients with known hypersensitivity to tetracaine hydrochloride or to drugs of a similar chemical configuration (ester-type local anesthetics), or aminobenzoic acid or its derivatives; and in patients for whom spinal anesthesia as a technique is contraindicated.
The decision as to whether or not spinal anesthesia should be used for an individual patient should be made by the physician after weighing the advantages with the risks and possible complications. Contraindications to spinal anesthesia as a technique can be found in standard reference texts, and usually include generalized septicemia, infection at the site of injection, certain diseases of the cerebrospinal system, uncontrolled hypotension, etc.

WARNINGS

RESUSCITATIVE EQUIPMENT AND DRUGS SHOULD BE IMMEDIATELY AVAILABLE WHENEVER ANY LOCAL ANESTHETIC DRUG IS USED.

Large doses of local anesthetics should not be used in patients with heartblock.

Reactions resulting in fatality have occurred on rare occasions with the use of local anesthetics, even in the absence of a history of hypersensitivity.

Methemoglobinemia
Cases of methemoglobinemia have been reported in association with local anesthetic use. Although all patients are at risk for methemoglobinemia, patients with glucose-6-phosphate dehydrogenase deficiency, congenital or idiopathic methemoglobinemia, cardiac or pulmonary compromise, infants under 6 months of age, and concurrent exposure to oxidizing agents or their metabolites are more susceptible to developing clinical manifestations of the condition. If local anesthetics must be used in these patients, close monitoring for symptoms and signs of methemoglobinemia is recommended.

Signs and symptoms of methemoglobinemia may occur immediately or may be delayed some hours after exposure and are characterized by a cyanotic skin discoloration and abnormal coloration of the blood. Methemoglobin levels may continue to rise; therefore, immediate treatment is required to avert more serious central nervous system and cardiovascular adverse effects, including seizures, coma, arrhythmias, and death. Discontinue tetracaine hydrochloride and any other oxidizing agents. Depending on the severity of the symptoms, patients may respond to supportive care, i.e., oxygen therapy, hydration. More severe symptoms may require treatment with methylene blue, exchange transfusion, or hyperbaric oxygen.

PRECAUTIONS:

The safety and effectiveness of any spinal anesthetic depend upon proper dosage, correct technique, adequate precautions, and readiness for emergencies. The lowest dosage that results in effective anesthesia should be used to avoid high plasma levels and serious systemic side effects. Tolerance varies with the status of the patient; debilitated, elderly patients or acutely ill patients should be given reduced doses commensurate with their weight, age, and physical status. Reduced doses are also indicated for obstetric patients and those with increased intra-abdominal pressure.

Caution should be used in administering tetracaine hydrochloride to patients with abnormal or reduced levels of plasma esterases.

Blood pressure should be frequently monitored during spinal anesthesia and hypotension immediately corrected.

Spinal anesthetics should be used with caution in patients with severe disturbances of cardiac rhythm, shock, and heartblock.

Drug Interactions: Tetracaine hydrochloride should not be used if the patient is being treated with a sulfonamide because aminobenzoic acid inhibits the action of sulfonamides.

Patients that are administered local anesthetics may be at increased risk of developing methemoglobinemia when concurrently exposed to the following oxidizing agents:

Class | Examples
Nitrates/Nitrites | nitroglycerin, nitroprusside, nitric oxide, nitrous oxide
Local anesthetics | benzocaine, lidocaine, bupivacaine, mepivacaine, tetracine, prilocaine, procaine, articaine, ropivacaine
Antineoplastic agents | cyclophosphamide, flutamide, rasburicase, ifosfamide, hydroxyurea
Antibiotics | dapsone, sulfonamides, nitrofurantoin, para-aminosalicylic acid
Antimalarials | chloroquine, primaquine
Anticonvulsants | phenytoin, sodium valproate, phenobarbital
Other drugs | Acetaminophen, metoclopramide, sulfa drugs (i.e., sulfasalazine), quinine

Carcinogenesis, Mutagenesis, Impairment of Fertility: There have been no long-term animal studies to evaluate carcinogenic potential and reproduction studies in animals. There is no evidence from human data that tetracaine hydrochloride may be carcinogenic or that it impairs fertility.

Pregnancy Category C: There have been no animal reproduction studies conducted with tetracaine hydrochloride. It is not known whether tetracaine hydrochloride can cause fetal harm when administered to a pregnant woman or can affect reproduction capacity. Tetracaine hydrochloride should be given to a pregnant woman only if clearly needed and the potential benefits outweigh the risk.

Labor and Delivery: Vasopressor agents administered for the treatment of hypotension resulting from spinal anesthesia may result in severe persistent hypertension and/or rupture of cerebral blood vessels if oxytocic drugs have also been administered; therefore, vasopressors should be used with extreme caution in the presence of oxytocic drugs.

Tetracaine hydrochloride has a recognized use during labor and delivery; the effect of the drug on duration of labor, incidence of forceps delivery, status of the newborn, and later growth and development of the child have not been studied.

Nursing Mothers: It is not known whether tetracaine hydrochloride is excreted in human milk; however, it is rapidly metabolized following absorption into the plasma. Because many drugs are excreted in human milk, caution should be exercised when tetracaine hydrochloride is administered to a nursing woman.

Pediatric Use: Safety and effectiveness of tetracaine hydrochloride in pediatric patients have not been established.

ADVERSE REACTIONS

Systemic adverse reactions to tetracaine hydrochloride are characteristic of those associated with other local anesthetics and can involve the central nervous system and the cardiovascular system. Systemic reactions usually result from high plasma levels due to excessive dosage, rapid adsorption, or inadvertent intravascular injection.

A small number of reactions to tetracaine hydrochloride may result from hypersensitivity, idiosyncrasy or diminished tolerance to normal dosage.

Central nervous system effects are characterized by excitation or depression. The first manifestation may be nervousness, dizziness, blurred vision, or tremors, followed by drowsiness, convulsions, unconsciousness and possibly respiratory and cardiac arrest. Since excitement may be transient or absent, the first manifestation may be drowsiness, sometimes merging into unconsciousness and respiratory and cardiac arrest. Other central nervous system effects may be nausea, vomiting, chills, constriction of the pupils, or tinnitus.

Cardiovascular system reactions include depression of the myocardium, blood pressure changes (usually hypotension), and cardiac arrest.

Allergic reactions, which may be due to hypersensitivity, idiosyncrasy, or diminished tolerance, are characterized by cutaneous lesions (eg. urticaria), edema, and other manifestations of allergy. Detection of sensitivity by skin testing is of limited value. Severe allergic reactions including anaphylaxis have rarely occurred and are not usually dose-related.

Reactions Associated with Spinal Anesthesia Techniques: Central Nervous System: post-spinal headache, meningismus, arachnoiditis, palsies, or spinal nerve paralysis. Cardiovascular: hypotension due to vasomotor paralysis and pooling of the blood in the venous bed. Respiratory: respiratory impairment or paralysis due to the level of anesthesia extending to the upper thoracic and cervical segments.

Gastrointestinal: nausea and vomiting.

Treatment of Reactions: Toxic effects of local anesthetics require symptomatic treatment; there is no specific cure. The most important measure is oxygenation of the patient by maintaining an airway and supporting ventilation. Supportive treatment of the cardiovascular system includes intravenous fluids and, when appropriate, vasopressors (preferably those that stimulate the myocardium). Convulsions are usually controlled with adequate oxygenation alone but intravenous administration in small increments of a barbiturate (preferably an ultrashort-acting barbiturate such as thiopental and thiamylal), or diazepam can be utilized. Intravenous barbiturates or anticonvulsant agents should only be administered by those familiar with their use and only if ventilation and oxygenation have first been assured. In spinal anesthesia, sympathetic blockade also occurs as a pharmacological action, resulting in peripheral vasodilation and often hypotension. The extent of the hypotension will usually depend on the number of dermatomes blocked. The blood pressure should therefore be monitored in the early phases of anesthesia. If hypotension occurs, it is readily controlled by vasoconstrictors administered either by the intramuscular or the intravenous route, the dosage of which would depend on the severity of the hypotension and the response to treatment.

Dosage and Administration

As with all anesthetics, the dosage varies and depends upon the area to be anesthetized, the number of neuronal segments to be blocked, individual tolerance, and the technique of anesthesia. The lowest dosage needed to provide effective anesthesia should be administered. For specific techniques and procedures, refer to standard textbooks.

Suggested Dosage for Spinal Anesthesia Using 1% Tetracaine HCl Injection, USP
Extent of Anesthesia | Dose of solution (mL) | Volume of spinal fluid (mL) | Site of injection (lumbar interspace)
Perineum | 0.5 (= 5 mg)* | 0.5 | 4th
Perineum and lower extremities | 1.0 (= 10 mg) | 1.0 | 3rd or 4th
Up to costal margin(= 15 mg to 20 mg)** | 1.5 to 2.0 | 1.5 to 2.0 | 2nd, 3rd, or 4th

* For vaginal delivery (saddle block), from 2 mg to 5 mg in dextrose.

**Doses exceeding 15 mg are rarely required and should be used only in exceptional cases. Inject solution at rate of about 1 mL per 5 seconds.

The extent and degree of spinal anesthesia depend upon dosage, specific gravity of the anesthetic solution, volume of solution used, force of the injection, level of puncture, position of the patient during and immediately after injection, etc.

When spinal fluid is added to 1% tetracaine hydrochloride injection, some turbidity results, the degree depending on the pH of the spinal fluid, the temperature of the solution during mixing, as well as the amount of drug and diluent employed. Liberation of base (which is completed within the spinal canal) is held to be essential for satisfactory results with any spinal anesthetic.

The specific gravity of spinal fluid at 25°C/25°C varies under normal conditions from 1.0063 to 1.0075. The 1% concentration in saline solution has a specific gravity of 1.0060 to 1.0074 at 25°C/25°C.

A hyperbaric solution may be prepared by mixing equal volumes of the 1% solution and Dextrose Solution 10%.

Examine vials carefully before use. Do not use solution if crystals, cloudiness, or discoloration is observed.

This formulation of tetracaine hydrochloride does not contain antimicrobial or bacteriostatic agents; therefore, unused portions should be discarded.

Sterilization of Vials
The tetracaine hydrochloride injection is sterile within an undamaged vial. To destroy bacteria on the exterior of vials use heat sterilization (autoclaving) before opening. Immersion in antiseptic solution is not recommended.

Autoclave at 15-pounds pressure, at 121°C (250°F), for 15 minutes.

Autoclaving increases likelihood of crystal formation. Unused autoclaved vials should be discarded. Under no circumstances should unused vials which have been autoclaved be returned to stock.

HOW SUPPLIED:

1% isotonic isobaric solution: 2 mL vials, box of 10.

NDC 54288-127-10

Storage: Store under refrigeration. Protect vials from light.

PATIENT COUNSELING INFORMATION

Inform patients that use of local anesthetics may cause methemoglobinemia, a serious condition that must be treated promptly. Advise patients or caregivers to stop use and seek immediate medical attention if they or someone in their care experience the following signs or symptoms: pale, gray, or blue colored skin (cyanosis); rapid heart rate; shortness of breath; lightheadedness; or fatigue.

Manufactured by:

BPI LABS LLC

12393 Belcher Rd, Suite 450,

Largo FL 33773

Rev.03/2020

Printed in USA

R-2003

LI16I

Package Label Principal Display Panel

Carton:

NDC 54288-127-10

TETRACAINE 1%

Tetracaine HCl Injection, USP

20 mg/2 mL (10 mg/mL

10 Vials (2 mL each)

Rx only

R-2306

LI127C-10

Label:

NDC 54288-127-01

TETRACAINE 1%

Tetracaine HCl Injection, USP

20 mg/2 mL (10 mg/mL)

Single Use Vial

Rx only

R-2507

LI127L-01